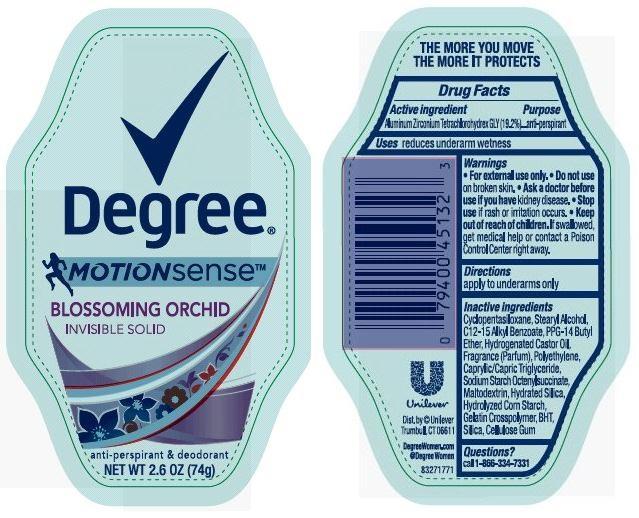 DRUG LABEL: Degree
NDC: 64942-1399 | Form: STICK
Manufacturer: Conopco Inc. d/b/a Unilever
Category: otc | Type: HUMAN OTC DRUG LABEL
Date: 20141203

ACTIVE INGREDIENTS: Aluminum Zirconium Tetrachlorohydrex GLY 19.2 g/100 g
INACTIVE INGREDIENTS: CYCLOMETHICONE 5; PPG-14 BUTYL ETHER; STEARYL ALCOHOL; HYDROGENATED CASTOR OIL; STARCH, CORN; BUTYLATED HYDROXYTOLUENE; HYDRATED SILICA; MALTODEXTRIN; SILICON DIOXIDE; CARBOXYMETHYLCELLULOSE SODIUM

Degree Motion Sense Blossoming Orchid antiperspirant deodorant

Active Ingredient

Aluminum Zirconium Tetrachlorohydrex GLY (19.2%)

Purpose
antiperspirant

Uses
reduces underarm wetness

Warnings
For external use only

Do not use on broken skin

Ask a doctor before use if you have kidney disease

Stop use if rash or irritation occurs

Keep out of reach of children. If swallowed, get medical help or contact a Poison Control Center right away.

Directions

apply to underarms only

INACTIVE INGREDIENT

Inactive ingredients Cyclopentasiloxane, Stearyl Alcohol, C12-15 Alkyl Benzoate, PPG-14 Butyl Ether, Hydrogenated Castor Oil, Fragrance (Parfum), Polyethylene, Caprylic/Capric Triglyceride, Sodium Starch Octenylsuccinate, Maltodextrin, Hydrated Silica, Hydrolyzed Corn Starch, Gelatin Crosspolymer, BHT, Silica, Cellulose Gum

Questions?
Call toll-free 1-866-334-7331